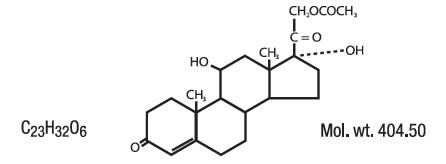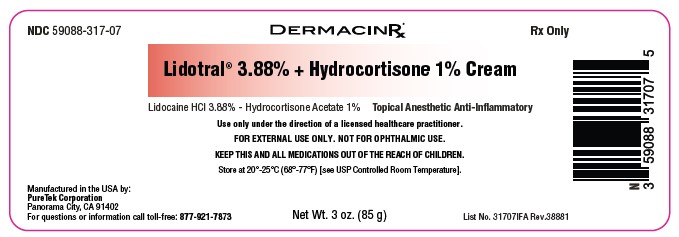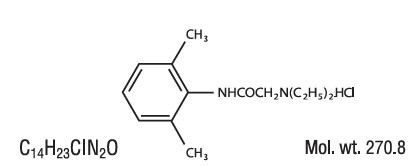 DRUG LABEL: Lidotral 3.88 Percent Plus Hydrocortisone 1 Percent Cream
NDC: 59088-317 | Form: CREAM
Manufacturer: PureTek Corporation
Category: prescription | Type: HUMAN PRESCRIPTION DRUG LABEL
Date: 20240603

ACTIVE INGREDIENTS: LIDOCAINE HYDROCHLORIDE 38.8 mg/1 g; HYDROCORTISONE ACETATE 10 mg/1 g
INACTIVE INGREDIENTS: PETROLATUM; ALUMINUM SULFATE; C13-16 ISOPARAFFIN; CETYL ALCOHOL; 1,2-HEXANEDIOL; CALCIUM ACETATE; PROPYLENE GLYCOL; MINERAL OIL; ETHYLHEXYLGLYCERIN; PEG-100 STEARATE; SORBITAN MONOSTEARATE; STEARYL ALCOHOL; STEARIC ACID; GLYCERYL MONOSTEARATE; GLYCERIN; WATER; BENZYL ALCOHOL; HEPTYL UNDECYLENATE; TRISODIUM CITRATE DIHYDRATE; SODIUM HYDROXIDE

Lidotral 3.88% + Hydrocortisone 1% Cream

Lidocaine HCI 3.88% - Hydrocortisone Acetate 1%

Lidotral® 3.88% + Hydrocortisone 1% Cream Each gram contains Lidocaine HCl 38.8 mg, Hydrocortisone Acetate 10 mg in a vehicle with Aqua (Purified Water), Aluminum Sulfate, Benzyl Alcohol, C13-16 Isoalkane, Calcium Acetate, Cetyl Alcohol, Ethylhexylglycerin, Glycerin, Glyceryl Stearate, 1,2-Hexanediol, Heptyl Undecylenate, Mineral Oil, PEG-100 Stearate, Petrolatum, Propylene Glycol, Sodium Citrate, Sodium Hydroxide, Sorbitan Stearate, Stearic Acid, Stearyl Alcohol.

DESCRIPTION:

Lidocaine HCl is chemically designated as acetamide, 2-(diethylamino)-N-(2,6-dimethylphenyl), and has the following structure:

Hydrocortisone acetate has a chemical name pregn-4-ene-3, 20-dione, 21-(acetyloxy)-11, 17-dihydroxy-(11β)-, It has the following structural formula:

CLINICAL PHARMACOLOGY:

Mechanism of Action: Product releases lidocaine to stabilize the neuronal membrane by inhibiting the ionic fluxes required for initiation and conduction of impulses, thereby affecting local anesthetic action. Hydrocortisone acetate provides relief of inflammatory and pruritic manifestations of corticosteroid responsive dermatoses.

PHARMACOKINETICS

Pharmacokinetics: Lidocaine may be absorbed following topical administration to mucous membranes, its rate and extent of absorption depending upon the specific site of application, duration of exposure, concentration, and total dosage. In general, the rate of absorption of local anesthetic agents following topical application occurs most rapidly after intratracheal administration. Lidocaine is also well-absorbed from the gastrointestinal tract, but little intact drug appears in the circulation because of biotransformation in the liver.

Lidocaine is metabolized rapidly by the liver, and metabolites and unchanged drug are excreted by the kidneys. Biotransformation includes oxidative N-dealkylation, ring hydroxylation, cleavage of the amide linkage, and conjugation. N-dealkylation, a major pathway of biotransformation, yields the metabolites monoethylglycinexylidide and glycinexylidide. The pharmacological/toxicological actions of these metabolites are similar to, but less potent than, those of lidocaine. Approximately 90% of lidocaine administered is excreted in the form of various metabolites, and less than 10% is excreted unchanged. The primary metabolite in urine is a conjugate of 4-hydroxy-2, 6-dimethylaniline.

The plasma binding of lidocaine is dependent on drug concentration, and the fraction bound decreases with increasing concentration. At concentrations of 1 to 4 g of free base per mL, 60 to 80 percent of lidocaine is protein bound. Binding is also dependent on the plasma concentration of the alpha-1-acid glycoprotein. Lidocaine crosses the blood-brain and placental barriers, presumably by passive diffusion.

Studies of lidocaine metabolism following intravenous bolus injections have shown that the elimination half-life of this agent is typically 1.5 to 2 hours. Because of the rapid rate at which lidocaine is metabolized, any condition that affects liver function may alter lidocaine kinetics. The half-life may be prolonged two-fold or more in patients with liver dysfunction. Renal dysfunction does not affect lidocaine kinetics but may increase the accumulation of metabolites.

Factors such as acidosis and the use of CNS stimulants and depressants affect the CNS levels of lidocaine required to produce overt systemic effects. Objective adverse manifestations become increasingly apparent with increasing venous plasma levels above 6 g free base per mL. In the rhesus monkey arterial blood levels of 18-21 g/mL have been shown to be the threshold for convulsive activity.

The extent of percutaneous absorption of topical corticosteroids is determined by many factors including the vehicle, the integrity of the epidermal barrier, and the use of occlusive dressings.

Topical corticosteroids can be absorbed from normal intact skin. Inflammation and/or other disease processes in the skin increase percutaneous absorption. Occlusive dressings substantially increase the percutaneous absorption of topical corticosteroids. Thus, occlusive dressings may be a valuable therapeutic adjunct for treatment of resistant dermatoses.

Once absorbed through skin, topical corticosteroids are handled through pharmacokinetic pathways similar to systemically administered corticosteroids. Corticosteroids are bound to plasma protein in varying degrees. Corticosteroids are metabolized primarily in the liver and are then excreted by the kidneys. Some of the topical corticosteroids and their metabolites are also excreted into the bile.

INDICATIONS:

For the temporary relief of pain and itching associated with minor burns, sunburns or minor skin irritations or hemorrhoids and itching associated with inflammation, and rashes due to eczema.

CONTRAINDICATIONS:

Product should not be used in patients with a history of sensitivity to any of its ingredients or adverse reactions to lidocaine or amide anesthetics, which usually do not cross-react with “caine” ester type anesthetics. If excessive irritation and significant worsening occur, discontinue use and seek the advice of your physician. Product and topical lidocaine should be used cautiously in those with impaired liver function, as well as the very ill or very elderly and those with significant liver disease. Product should be used with caution in patients receiving antiarrhythmic drugs of Class I since the adverse effects are additive and generally synergistic. Product is contraindicated for tuberculous or fungal lesions or skin vaccinia, varicella and acute herpes simplex. Topical corticosteroids are contraindicated in those patients with a history of hypersensitivity to any of the components of the preparation.

WARNINGS/PRECAUTIONS:

WARNINGS:

CONCERNS RELATED TO ADVERSE EFFECTS:
Methemoglobinemia:Has been reported with local anesthetics; clinically significant methemoglobinemia requires immediate treatment along with discontinuation of the anesthetic and other oxidizing agents. Onset may be immediate or delayed (hours) after anesthetic exposure. Patients with G6PD deficiency, congenital or idiopathic methemoglobinemia, cardiac or pulmonary compromise, exposure to oxidizing agents or their metabolites, or infants <6 months of age are more susceptible and should be closely monitored for signs and symptoms of methemoglobinemia (including pale, gray, or blue-colored skin (cyanosis), headache, rapid pulse, shortness of breath, lightheadedness, fatigue).

WARNINGS: For external use only. Not for ophthalmic use.

Topical formulations of lidocaine may be absorbed to a greater extent through mucous membranes and abraded, fissured or irritated skin than through intact skin. Product should not be ingested or applied into the mouth, inside of the nose or in the eyes. Product should not be used in the ears. Any situation where lidocaine penetrates beyond the tympanic membrane into the middle ear is contraindicated because of ototoxicity associated with lidocaine observed in animals when instilled in the middle ear. Product should not come into contact with the eye or be applied into the eye because of the risk of severe eye irritation and the loss of eye surface sensation, which reduces protective reflexes and can lead to corneal irritation and possibly abrasion. If eye contact occurs, rinse out the eye immediately with saline or water and protect the eye surface until sensation is restored.

PRECAUTIONS:

If irritation or sensitivity occurs or infection appears, discontinue use and institute appropriate therapy. If extensive areas are treated, the possibility of systemic absorption exists. Systemic absorption of topical steroids has produced reversible hypothalamic-pituitary-adrenal (HPA) axis suppression, manifestation of Cushing’s syndrome, hyperglycemia, and glycosuria in some patients. Conditions which augment systemic absorption include the application of the more potent steroids, use over large surface areas, prolonged use, and the addition of occlusive dressings. Therefore, patients receiving a large dose of potent topical steroids applied to a large surface area, or under an occlusive dressing, should be evaluated periodically for evidence of HPA axis suppression. If noted, an attempt should be made to withdraw the drug, to reduce the frequency of application, or to substitute a less potent steroid. Recovery of the HPA axis function is generally prompt and complete upon discontinuation of the drug. Infrequently, signs and symptoms of steroid withdrawal may occur, requiring supplemental systemic corticosteroids. Children may absorb proportionately larger amounts of topical corticosteroids and thus be more susceptible to systemic toxicity. If irritation develops, topical steroids should be discontinued and appropriate therapy instituted. In the presence of dermatological infections, the use of an appropriate antifungal or antibacterial agent should be instituted. If a favorable response does not occur promptly, the corticosteroid should be discontinued until the infection has been adequately controlled.

Carcinogenesis, Mutagenesis and Impairment of Fertility:

Long-term animal studies have not been performed to evaluate the carcinogenic potential or the effect on fertility of topical corticosteroids. Studies to determine mutagenicity with prednisolone and hydrocortisone have revealed negative results. Studies of lidocaine in animals to evaluate the carcinogenic and mutagenic potential of the effect on fertility have not been conducted.

Use in Pregnancy:

Teratogenic Effects:

Pregnancy Category C. Reproduction studies have been performed for lidocaine in rats at doses up to 6.6 times the human dose and have revealed no evidence of harm to the fetus caused by lidocaine. There are, however, no adequate and well-controlled studies in pregnant women. Animal reproduction studies are not always predictive of human response. General consideration should be given to this fact before administering lidocaine to women of childbearing potential, especially during early pregnancy when maximum organogenesis takes place. Corticosteroids are generally teratogenic in laboratory animals when administered systemically at relatively low dosage levels. The more potent corticosteroids have been shown to be teratogenic after dermal application in laboratory animals. There are no adequate and well controlled studies in pregnant women on teratogenic effects from topically applied corticosteroids. Therefore, topical corticosteroids should be used during pregnancy only if the potential benefit justifies the potential risk to the fetus. Drugs of this class should not be used extensively on pregnant patients, in large amounts, or for prolonged periods of time.

NURSING MOTHERS:

It is not known whether this drug is excreted in human milk. Because many drugs are excreted in human milk, caution should be exercised when this drug is administered to a nursing mother.

PEDIATRIC USE:

Safety and efficacy in children have not been established.

ADVERSE REACTIONS:

During or immediately following application of product, there may be transient stinging or burning from open areas of skin, or transient blanching (lightening), or erythema (redness) of the skin.

DOSAGE AND ADMINISTRATION:

Apply product to the affected area(s) twice daily or as directed by a licensed healthcare practitioner. If the condition does not respond to repeated courses of product or should worsen, discontinue use and seek the advice of your physician. Wash hands before and after application.

HOW SUPPLIED:

Lidotral® 3.88% + Hydrocortisone 1% Cream (Lidocaine HCl 3.88% - Hydrocortisone Acetate 1%) is supplied as an off-white cream in a 3 oz. (85 g) tube with CRC Cap - NDC 59088-317-07

KEEP THIS AND ALL MEDICATIONS OUT OF REACH OF CHILDREN.

Store at 20º-25ºC (68º-77ºF) [see USP Controlled Room Temperature].

Lidotral® 3.88% + Hydrocortisone 1% Cream

Manufactured in the USA by:
PureTek Corporation
Panorama City, CA 91402
For questions or information
call toll-free: 877-921-7873